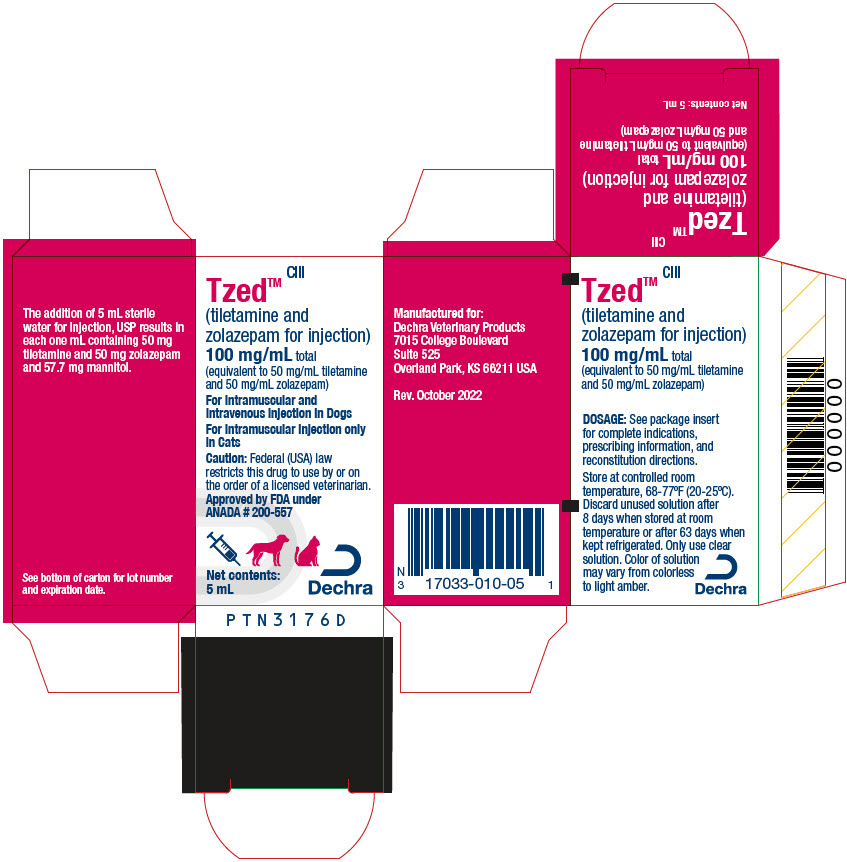 DRUG LABEL: Tzed
NDC: 17033-010 | Form: INJECTION, POWDER, LYOPHILIZED, FOR SOLUTION
Manufacturer: Dechra Veterinary Products LLC
Category: animal | Type: PRESCRIPTION ANIMAL DRUG LABEL
Date: 20260217
DEA Schedule: CIII

ACTIVE INGREDIENTS: Tiletamine Hydrochloride 50 mg/1 mL; Zolazepam Hydrochloride 50 mg/1 mL

Tzed™ CIII
(tiletamine and zolazepam for injection)

100 mg/mL total (equivalent to 50 mg/mL tiletamine and 50 mg/mL zolazepam)

For Intramuscular and Intravenous injection in Dogs

For Intramuscular injection only in Cats

CAUTION

Federal (USA) law restricts this drug to use by or on the order of a licensed veterinarian.

DESCRIPTION

Tzed (tiletamine and zolazepam for injection) is a nonnarcotic, nonbarbiturate, injectable anesthetic agent for dogs and cats. Chemically, Tzed is a combination of equal parts by weight of base of tiletamine hydrochloride (2-[ethylamino]-2-[2-thienyl]-cyclohexanone hydrochloride), an arylaminocycloalkanone dissociative anesthetic, and zolazepam hydrochloride (4-[o-ﬂuorophenyl]-6, 8-dihydro-1,3,8-trimethylpyrazolo [3, 4-e] [1,4] diazepin-7 [1H]-1- hydrochloride), a non-phenothiazine diazepinone having minor tranquilizing properties. The product is supplied sterile in vials. The addition of 5 mL diluent produces a solution containing the equivalent of 50 mg tiletamine base, 50 mg zolazepam base and 57.7 mg mannitol per milliliter. This solution has a pH of 2 to 3.5 and is recommended for deep intramuscular injection.

INDICATIONS

Dogs: Tzed is indicated in dogs for restraint and minor procedures of short duration (30 min. avg.) requiring mild to moderate analgesia. Minor surgery is considered to be laceration repair, draining of abscesses, castrations and other procedures requiring mild to moderate analgesia. (See Dogs under Dosage and Administration.) Tzed administered intravenously is indicated in dogs for induction of anesthesia followed by maintenance with an inhalant anesthetic.

Cats: Tzed is indicated in cats for restraint or for anesthesia combined with muscle relaxation.

DOSAGE AND ADMINISTRATION

The dose is determined by the total combined concentration of 100 mg/mL (see HOW SUPPLIED)

Dogs:

Intramuscular (IM) For Restraint and Minor Procedures of Short Duration Requiring Mild to Moderate Analgesia:

In healthy dogs, an initial intramuscular dosage of 3 to 4.5 mg/lb (6.6 to 9.9 mg/kg) Tzed is recommended for diagnostic purposes; 4.5 to 6 mg/lb (9.9 to 13.2 mg/kg) for minor procedures of short duration, such as treatment of lacerations and wounds, castrations and other procedures requiring mild to moderate analgesia. When supplemental doses of Tzed are required, such individual supplemental doses should be less than the initial dose, and the total dose given (initial dose plus supplemental dose or doses) should not exceed 12 mg/lb (26.4 mg/kg). The maximum safe dose is 13.6 mg/lb (29.92 mg/kg). (See Animal Safety.) Results from Tzed anesthesia in dogs will be more satisfactory if the procedures are completed within one hour and if the procedures can be completed following single dose administration. In order to maintain at least a 2× margin of safety in dogs, the use of this product is limited to procedures that call for low doses (see Indications). Studies show that there is variation in response to different dosages of tiletamine and zolazepam and that low doses do not give adequate levels of anesthesia, and in some instances do not give adequate analgesia, for extensive procedures.

Intravenous (IV) For Induction of Anesthesia Followed by Maintenance with an Inhalant Anesthetic:

In dogs, for induction of anesthesia, administer Tzed intravenously at 1-2 mg/lb (2.2-4.4 mg/kg) body weight to effect. Tzed should be administered slowly, over 30-45 seconds; after approximately 30-60 seconds, the dog's level of consciousness, muscle relaxation, and jaw tone should be assessed to determine the ability to intubate. If after waiting 60 seconds the dog's level of anesthesia is not sufﬁcient for successful intubation, additional Tzed may be administered; the total dose should not exceed 2 mg/lb (4.4 mg/kg) body weight.

Cats:

In healthy cats, an initial Tzed dosage of 4.4 to 5.4 mg/lb (9.7 to 11.9 mg/kg) IM is recommended for such procedures as dentistry, treatment of abscesses, foreign body removal and related types of surgery; 4.8 to 5.7 mg/lb (10.6 to 12.5 mg/kg) for minor procedures requiring mild to moderate analgesia, such as repair of lacerations, castrations and other procedures of short duration. Initial dosages of 6.5 to 7.2 mg/lb (14.3 to 15.8 mg/kg) are recommended for ovariohysterectomy and onychectomy. When supplemental doses of Tzed are required, such individual supplemental doses should be given in increments that are less than the initial dose, and the total dose given (initial dose plus supplemental doses) should not exceed the maximum allowable safe dose of 32.7 mg/lb (72 mg/kg). (See Animal Safety.)

General Dosing Information: Fasting prior to induction of general anesthesia with Tzed is not essential; however, when preparing for elective surgery, it is advisable to withhold food for at least 12 hours prior to Tzed administration. As with other injectable anesthetic agents, the individual response to Tzed is somewhat varied, depending upon the dose, general physical condition and age of the patient, duration of the surgical procedure, and any preanesthetics used. Therefore, recommendations for dosage regimens cannot be ﬁxed absolutely. Speciﬁc dosage requirements must be determined by evaluation of the health status and condition of the patient and of the procedure to be performed.

Recovery varies with the age and physical condition of the animal and the dose of Tzed administered. Recovery is extended with high dose or multiple injections, particularly in cats.

Intramuscular injection in dogs and cats:

There may be pain on injection. This is especially prevalent in cats.

Following a single, deep intramuscular injection of Tzed in cats and dogs, onset of anesthetic effect usually occurs within 5 to 12 minutes. Muscle relaxation is optimum for approximately the ﬁrst 20 to 25 minutes after Tzed is administered, and then diminishes.

Repeated doses increase the duration of the effect of Tzed but may not further diminish muscle tone. The quality of anesthesia with repeated doses varies because the ratio of the two components within the animal's body changes with each injection. This is due to the difference in the rates of metabolism and elimination of the two components. The quality of anesthesia will be improved and more predictable if the entire dose is given as a single injection rather than in several doses. The best method of evaluating the depth of Tzed anesthesia is to monitor the patient for deliberate conscious response to nociceptive stimuli.

If adequate anesthesia is not produced by the recommended dosage regimen, supplemental anesthesia or another agent is indicated. This includes the use of barbiturates and volatile anesthetics. When used concurrently with Tzed the dosage of these agents should be reduced.

PREPARATION OF SOLUTION FOR ADMINISTRATION

To each vial add 5 mL sterile water for injection, USP. Slight agitation will facilitate complete reconstitution. The resultant solution will contain 100 mg total Tzed per one milliliter (50 mg tiletamine and 50 mg zolazepam per mL).

Discard unused solution after 8 days when stored at room temperature or after 63 days when kept refrigerated. Only use clear solution. Color of solution may vary from colorless to light amber.

CONTRAINDICATIONS

The use of Tzed is contraindicated in dogs and cats with pancreatic disease. Tzed should not be used in dogs and cats with severe cardiac or pulmonary dysfunction.

Because the teratogenic potential of Tzed is unknown, it should not be used in pregnant bitches or queens at any stage of pregnancy. Also, a study has shown that tiletamine and zolazepam crosses the placental barrier and produces respiratory depression in the newborn; therefore, its use for Cesarean section is contraindicated.

WARNINGS

FOR USE IN DOGS AND CATS ONLY.

When using Tzed for induction of anesthesia, patients should be continuously monitored. Facilities for the maintenance of a patent airway, artiﬁcial ventilation and oxygen supplementation should be available.

Pulmonary edema has been reported to occur in cats with the use of tiletamine and zolazepam for injection. Signs and symptoms include dyspnea, lethargy, anorexia and abnormal behavior. Deaths have been reported occasionally in severely affected individuals. Cats should be observed closely for any signs and symptoms which may suggest pulmonary edema so that appropriate therapy may be instituted.

The principal route of excretion of both components in the cat is the urine; therefore, Tzed is not recommended for use in cats suffering from renal insufﬁciency.

Balance studies in dogs indicated extensive biotransformation of both components with less than 4% of the dose excreted unchanged in the urine.

Tzed is excreted predominantly by the kidneys. Preexistent renal pathology or impairment of renal function may be expected to result in prolonged duration of anesthesia.

Phenothiazine-derivative drugs should not be used with Tzed at dosages indicated for intramuscular (IM) injection because the combination produces respiratory and myocardial depression, hypotension and hypothermia.

The safe use of Tzed in pregnant animals or on reproduction has not been established. Tzed crosses the placental barrier and causes respiratory depression in the neonate.

PRECAUTIONS

The dosage of Tzed should be reduced in geriatric dogs and cats, in animals in debilitated condition and in animals with impairment of renal function.

Death has occurred in both cats and dogs following intramuscular tiletamine and zolazepam administration. Preexisting pulmonary disease, renal disease (see Contraindications and Warnings) and shock were causally implicated at necropsy; however, death was drug attributable in at least one dog (of 1072) and one cat (of 1095).

Intravenous tiletamine and zolazepam has been demonstrated to be safe in a ﬁeld study in dogs when used in conjunction with phenothiazine-derivative drugs (acepromazine) administered at dosages from 0.04-0.06 mg/kg IM.

Cats and smaller dogs with small body masses in relation to large body surfaces should be protected from heat loss during Tzed anesthesia. Body temperature should be monitored, and supplemental heat may be required to control hypothermia. As with other anesthetics, it is prudent to provide for hemostasis during any surgical procedure.

During Tzed anesthesia, athetoid movement may occur. This athetosis should not be mistaken for lack of anesthesia nor is it indicative of lack of analgesia. Do not give additional anesthesia in an attempt to abolish the athetoid movement. Efforts to eliminate athetoid movement with additional doses of Tzed can result in anesthetic overdosage.

Tzed does not abolish laryngeal, pharyngeal, pinnal, palpebral, and pedal reﬂexes, and may not be adequate as the sole anesthetic for surgical procedures in these areas. Endotracheal tubes are not well tolerated in connection with Tzed anesthesia in the cat and their use may result in impaired respiration. After removal of the tube, normal respiration should resume.

The stimulation of surgical procedures aids in maintaining adequate ventilation. The anesthetized patient must be monitored throughout the procedure, and if cardiopulmonary problems do occur, measures must be taken to assure that alveolar ventilation and cardiovascular functions are maintained.

The eyes normally remain open with the pupils dilated. The use of a bland ophthalmic ointment is advisable to protect the corneas from desiccation. The concurrent use of chloramphenicol will prolong the duration of anesthesia in cats.

Copious salivation may occur during Tzed anesthesia. Ptyalism may be controlled in dogs and cats by administering atropine sulfate, USP, 0.02 mg/lb (0.04 mg/kg) body weight (IV, IM, or SC) as concurrent medication. Exaggerated swallowing, reﬂex action and accumulation of saliva may give rise to vomiting and retching.

ADVERSE REACTIONS

For Restraint and Minor Procedures of Short Duration Requiring Mild to Moderate Analgesia

Respiratory depression may occur following administration of high doses of Tzed. If at any time respiration becomes excessively depressed and the animal becomes cyanotic, resuscitative measures should be instituted promptly. Adequate pulmonary ventilation using either oxygen or room air is recommended as a resuscitative measure.

Adverse reactions reported include emesis during emergence, excessive salivation, transient apnea, vocalization, erratic recovery and prolonged recovery, excessive tracheal and bronchial secretions when atropine sulfate was not given before anesthesia, involuntary muscular twitching, hypertonicity, cyanosis, cardiac arrest, pulmonary edema and muscle rigidity during surgical procedures. Central nervous system stimulation and convulsions have also been reported. Tachycardia frequently occurs, particularly in the dog. This rise in heart rate usually lasts about 30 minutes. Either hypertension or hypotension may also occur. Insufﬁcient anesthesia has been reported in dogs.

Death has been reported in dogs and cats following tiletamine and zolazepam administration.

Intravenous Induction of Anesthesia followed by Maintenance with Inhalant Anesthesia in Dogs

In a ﬁeld study to assess the effectiveness and safety of tiletamine and zolazepam administered intravenously at 1-2 mg/lb (2.2-4.4 mg/kg) for the induction of anesthesia followed by maintenance with inhalant anesthesia in dogs, 144 dogs were intravenously administered tiletamine and zolazepam (See Effectiveness). Sixteen adverse reactions occurred during the study: nystagmus (5), emesis (4), diarrhea (2), and one occurrence each of hypersalivation, urticarial, anorexia, hyperthermia, and lethargy. All adverse reactions resolved by the end of the study.

Physiologic abnormalities related to general anesthesia were transient and not severe.

Post-induction apnea (time from induction to ﬁrst inspiration ≥30 seconds) was observed in 49.3% of dogs across all treatment groups with a mean duration of one minute. The highest overall frequency and duration of post-induction apnea was in the alpha2-agonist + opioid groups.

Overall, 36 dogs received assisted ventilation. Assisted ventilation was needed most frequently early in the procedure (at procedure start, possibly after an apneic period) then decreased in frequency as the procedure continued.

Sixteen dogs experienced oxygen saturation (SpO2) ≤90 mmHg: 7 in the alpha2-agonist + opioid groups, 6 in the phenothiazine + opioid groups, and 3 in the opioid alone groups.

Twenty-ﬁve dogs had a temperature ≥103°F during the study, with 12 of these occurring prior to preanesthetic administration only. Of the remaining 13 dogs, 7 were in the alpha2-agonist + opioid groups, 5 were in the opioid alone groups, and 1 in the phenothiazine + opioid groups. One dog was reported with hyperthermia as an adverse reaction in the alpha2-agonist + opioid treatment groups. The dog became excitable during recovery and its temperature elevated to 105.7°F. Hyperthermia resolved with treatment of IV ﬂuids and cooling.

Twenty-seven dogs experienced temperatures ≤96°F at one or more timepoints. Most dogs received supplemental heat during surgery.

Fifty-nine dogs had mean blood pressure (BP) values ≤60 mmHg. These values are spread among all treatment groups. No dogs were reported with adverse reactions due to hypotension or hypertension in any dose groups. Elevated or low BP values were transient.

Ventricular premature depolarizations were noted in 3 dogs in the alpha2-agonist + opioid group. This transient rhythm disturbance is not uncommon in dogs receiving alpha2-agonists or inhalant anesthetics. One dog in the phenothiazine + opioid group showed transient ST depression that could have been due to cardiac hypoxia. All dogs recovered normally.

To report suspected adverse drug events, for technical assistance or to obtain a copy of the Safety Data Sheet (SDS), contact Dechra Veterinary Products at (866) 933-2472.

For additional information about adverse drug experience reporting for animal drugs, contact FDA at 1-888-FDA-VETS or online at http://www.fda.gov/reportanimalae.

CLINICAL PHARMACOLOGY

Mechanism of Action

Tzed (tiletamine and zolazepam for injection) is a rapid-acting anesthetic combination of tiletamine hydrochloride and zolazepam hydrochloride. Tiletamine hydrochloride is a dissociative anesthetic agent whose pharmacologic action is characterized by profound analgesia, normal pharyngeal-laryngeal reﬂexes and cataleptoid anesthesia. The anesthetic state produced does not ﬁt into the conventional classiﬁcation of stages of anesthesia, but instead Tzed produces a state of unconsciousness which has been termed "dissociative" anesthesia in that it appears to selectively interrupt association pathways to the brain before producing somesthetic sensory blockade.

Cranial nerve and spinal reﬂexes remain active; however, these reﬂexes must not be confused with inadequate anesthesia. Analgesia results from apparent selective interruption of sensory inputs to the brain and usually persists after the anesthetic effect has subsided.

Protective reﬂexes, such as coughing and swallowing, are maintained under tiletamine anesthesia. Other reﬂexes, e.g., corneal, pedal, are maintained during tiletamine anesthesia, and should not be used as criteria for judging depth of anesthesia. The eyes normally remain open with the pupil dilated. It is suggested that a bland ophthalmic ointment be applied to the cornea if anesthesia is to be prolonged.

Used alone, tiletamine hydrochloride does not provide adequate muscle relaxation for abdominal surgical procedures. When combined with zolazepam hydrochloride, good muscle relaxation is generally attained during the phase of deep surgical anesthesia.

Pharmacokinetics

The pharmacokinetics of tiletamine and zolazepam injectable solution was evaluated in 12 healthy adult Beagle dogs, following a single intravenous (IV) administration of 2.2 mg/kg bodyweight, which is equivalent to 1.1 mg/kg for both tiletamine hydrochloride and zolazepam hydrochloride. After administration of 2.2 mg/kg tiletamine and zolazepam IV, the initial mean concentration of tiletamine (C0) was 1018 ng/mL, the systemic clearance (CL) was 6223 mL/kg/h, the area under the curve to the last measured concentration (AUC 0-last) was 178 ng*hr/mL, and steady state volume of distribution (Vss) was 3250 mL/kg. The mean elimination half-life of tiletamine was 0.87 hours. For zolazepam, the mean C0 was 2594 ng/mL, CL was 1993 mL/kg/h and Vss was 604 mL/kg. The mean elimination half-life of zolazepam was 0.41 hours. The mean C0 and AUC0-t(last) were approximately 2.5 and 3 times, respectively, greater for zolazepam than for tiletamine. However, the mean half-life (T1/2) of tiletamine was approximately 2.5 times longer than for zolazepam, resulting in quantiﬁable plasma concentrations up to 2 hours longer.

Pretreatment with an alpha2-agonist or phenothiazine followed by inhalant isoﬂurane has been shown to increase in the initial concentration of both tiletamine and zolazepam.

EFFECTIVENESS

Dogs

Preanesthesia

In a ﬁeld study conducted at 6 veterinary hospitals, 144 dogs of various breeds, ranging in age from 4 months to 14 years (mean age 5 years) and body weights from 1.2- 85.5 kg, were enrolled for completion of a veterinary procedure requiring anesthesia. Dogs were preanesthetized with a phenothiazine + opioid, an opioid alone, or an alpha2-agonist + opioid at the study Investigator's discretion based on individual patient needs. Approximately 20 minutes later, dogs were intravenously administered tiletamine and zolazepam at 1-2 mg/lb (2.2-4.4 mg/kg) 'to effect' of anesthesia and were intubated. After induction, dogs received either isoﬂurane or sevoﬂurane for anesthetic maintenance for at least 30 minutes. Procedures conducted included dental prophylaxis with or without extractions (64), ovariohysterectomy (31), castration (18), and mass removal (14). Upon completion of the procedure, dogs were monitored in recovery for 4 hours, then followed at home for 2-4 days, monitoring for the presence of abnormal clinical signs.

Of 144 dogs enrolled in the study, 142 (98.6%) were successfully intubated after intravenous administration of tiletamine and zolazepam at a mean dosage of 1.2 mg/lb (2.7 mg/kg). The mean dosage range was lowest in the alpha2-agonist + opioid preanesthetic treatment group (0.9 mg/lb; 2 mg/kg) and highest in the opioid alone preanesthetic group (1.8 mg/lb; 3.9 mg/kg).

Overall induction quality evaluated on a scale of acceptable, intermediate, or unacceptable was acceptable in 131/142 (91.6%) dogs and intermediate in 12/143(8.4%) dogs. On a scale of good, fair, or poor, study participants rated the quality of recovery from anesthesia as good in 75% of dogs (118/144) and fair in 18.1% (26/144). In an overall assessment of anesthesia, considering induction, maintenance, and recovery, was scored as excellent or good in 128/144 (88.9%) of dogs. Three dogs (2.1%) were rated with an overall assessment of anesthesia as poor, and for these dogs, recovery was also rated poor. Physiologic measurements of heart rate, respiratory rate, body temperature, oxygen saturation, and blood pressure during anesthetic induction, maintenance, and recovery showed that the administration of tiletamine and zolazepam did not severely impact these variables. A variety of concomitant treatments were used during the study including intravenous ﬂuid solutions, non-steroidal anti-inﬂammatory medications, antimicrobials, and antiparasitics that were consistent with routine canine practice.

ANIMAL SAFETY

Tiletamine and zolazepam for injection has a wider margin of safety in cats than in dogs. Dogs have survived repeated IM dosage regimens of 13.6 mg/lb (30 mg/kg) (maximum safe dose) for eight successive days. This is approximately two times the maximum recommended therapeutic dose. Cats have survived IM dosage regimens of up to 32.7 mg/lb (72 mg/kg) (maximum safe dose) on alternate days for seven episodes. This is 4.6 times the maximum recommended therapeutic dose for cats. However, these reports should not obviate prudent anesthetic practices. Some degree of tolerance has been reported. This tolerance appears to be species-variable.

Cats: In cats, the duration of effect of zolazepam exceeds that of tiletamine so that as the animal recovers there is a greater degree of tranquilization than anesthetization. There is a slight lowering of blood pressure during the ﬁrst hour after injection. Heart rate and electrocardiogram readings are unaffected by tiletamine and zolazepam for injection. Arterial pO2 levels are decreased three minutes after injection but usually return to normal within 15 to 35 minutes.

Dogs: In dogs, the duration of effect of tiletamine exceeds that of zolazepam so there is a lesser degree of tranquilization than anesthetization in this species. The total effect of tiletamine and zolazepam for injection in dogs is of shorter duration than in cats.

Following administration of tiletamine and zolazepam for injection in dogs, a marked, persistent tachycardia occurs within two minutes following either 4.5 or 9 mg/lb (10 or 20 mg/kg) tiletamine and zolazepam for injection intramuscularly. Stroke volume decreases proportionately to the increased rate at the 4.5 mg/lb (10 mg/kg) dose, with little change in net cardiac output. There is an initial increase in systolic blood pressure, with a slight drop in pressure within ﬁve minutes. The systolic blood pressure remains at this decreased level throughout the duration of the anesthetic effect. Diastolic pressure increases throughout this same period. Following a 9 mg/lb (20 mg/kg) dose of tiletamine and zolazepam for injection in dogs, the relationship between stroke volume and heart rate is disproportionate, with a resultant substantial decrease in cardiac output. Contractility and mean blood pressure are decreased, indicating direct myocardial depression. Ventricular function is adequate. During surgical manipulations, tachycardia and hypertension may be observed, and may be brought on by sympathetic reaction to painful stimuli. Epinephrine is markedly less arrhythmogenic in animals under tiletamine and zolazepam for injection anesthesia than in those under halothane anesthesia.

During tiletamine and zolazepam for injection anesthesia, the assurance of a patent airway is greatly enhanced by virtue of maintaining pharyngeal-laryngeal reﬂexes. During the ﬁrst 15 minutes after intramuscular administration of 9 mg/lb (20 mg/kg) of tiletamine and zolazepam for injection, the respiratory rate is doubled while the tidal volume is decreased to less than one-half of control values. Arterial pO2 levels also decrease. This may be evidenced by hypoxemia and cyanosis. The pulmonary function usually returns to normal within 35 minutes after the administration of tiletamine and zolazepam for injection.

Preanesthetic Compatibility Study in Dogs

Six healthy Beagle dogs (3 males and 3 females), at least 8 months of age, ranging in body weight between 5.6 and 9.4 kg, were ﬁtted with a telemetry device that captured systemic arterial blood pressures, electrocardiogram, and body temperature. Each dog received a total of 6 treatments with at least a 7-day washout between periods. During each period, dogs received 1 of the following 6 preanesthetics prior to the tiletamine and zolazepam administration: placebo (0.9% saline), acepromazine low dose (0.1 mg/kg body weight [BW]), acepromazine high dose (1.1 mg/kg BW), dexmedetomidine low dose (125 mcg/m^2 body surface area [BSA]), dexmedetomidine high dose (375 mcg/m^2 BSA), or butorphanol (0.4 mg/kg BW). Blood samples were collected at intubation, end of isoﬂurane administration, and after anesthesia when the dogs were able to walk. Plasma concentrations of tiletamine and zolazepam were measured using a validated method. Preanesthetic treatment with high dose acepromazine and both high and low doses of dexmedetomidine resulted in substantial increases in plasma concentrations of tiletamine and zolazepam at intubation. The increase in the tiletamine plasma concentrations was approximately 2× higher for the high dose of acepromazine and 2.7 to 4.5× higher for the low and high doses of dexmedetomidine, respectively, compared to saline. The increase in zolazepam plasma concentrations was 1.5× higher for the high dose acepromazine, and 1.8 to 2.8× higher for the low and high doses of dexmedetomidine, respectively, compared to saline.

No information on the dose-sparing of tiletamine and zolazepam was obtained during the study because the dogs were given the full initial half-dose (2.2 mg/kg) and not actually administered tiletamine and zolazepam 'to effect'. The average total dose of test article administered to the dogs was 2.6 mg/kg for the saline group and 2.2 mg/kg for the other treatment groups. One dog (saline group) required more than the initial 2.2 mg/kg bolus to achieve intubation at the ﬁrst attempt.

Without preanesthesia (saline group), dogs retained a strong cough reﬂex, chewing motions, tachycardia and increased muscle tone during intubation. With preanesthesia, half of the dogs in the high dose dexmedetomidine group had no laryngeal reﬂex response to intubation and all experienced post-intubation apnea. The post-intubation apnea suggests that the 2.2 mg/kg dose of tiletamine and zolazepam was higher than necessary in some groups.

All dogs in all treatment groups achieved successful anesthetic plane following tiletamine and zolazepam administration and were intubated and induced to isoﬂurane anesthesia uneventfully. The quality of intubation, and occurrence and severity of adverse reactions (e.g., apnea and bradypnea) following tiletamine and zolazepam administration and intubation revealed differences among preanesthetic treatment groups. The cardiovascular and respiratory changes observed were typical of each preanesthetic medication used in combination with tiletamine and zolazepam. Acepromazine and isoﬂurane administration decreased arterial blood pressure. Dexmedetomidine decreased heart rate. Intubation transiently increased heart rate and/or blood pressure (sympathetic stimulations). Mild to severe respiratory depression was observed after tiletamine and zolazepam administration and each preanesthetic agent. Adverse reactions were manageable with appropriate care.

STORAGE CONDITIONS

Store at controlled room temperature, 68-77°F (20-25°C). Discard unused solution after 8 days when stored at room temperature or after 63 days when kept refrigerated. Only use clear solution. Color of solution may vary from colorless to light amber.

HOW SUPPLIED

Tzed (tiletamine and zolazepam for injection) is available in individual vials of 5 mL solution when reconstituted. The addition of 5 mL diluent produces a solution containing the equivalent of 50 mg tiletamine base, 50 mg zolazepam base and 57.7 mg mannitol per milliliter.

NDC 17033-010-05: 100 mg/mL total (equivalent to 50 mg/mL tiletamine and 50 mg/mL zolazepam) when reconstituted

Approved by FDA under ANADA # 200-557

Manufactured for:
Dechra Veterinary Products
7015 College Boulevard, Suite 525
Overland Park, KS 66211 USA

PTN3199C

Rev. December 2020

PRINCIPAL DISPLAY PANEL - 5 mL Vial Carton

CIII

Tzed™
(tiletamine and zolazepam for injection)

100 mg/mL total
(equivalent to 50 mg/mL tiletamine and 50 mg/mL zolazepam)

For Intramuscular and Intravenous injection in Dogs

For Intramuscular injection only in Cats

Caution: Federal (USA) law restricts this drug to use by or on the order of a licensed veterinarian.

Approved by FDA under ANADA # 200-557

Net contents: 5 mL

Dechra